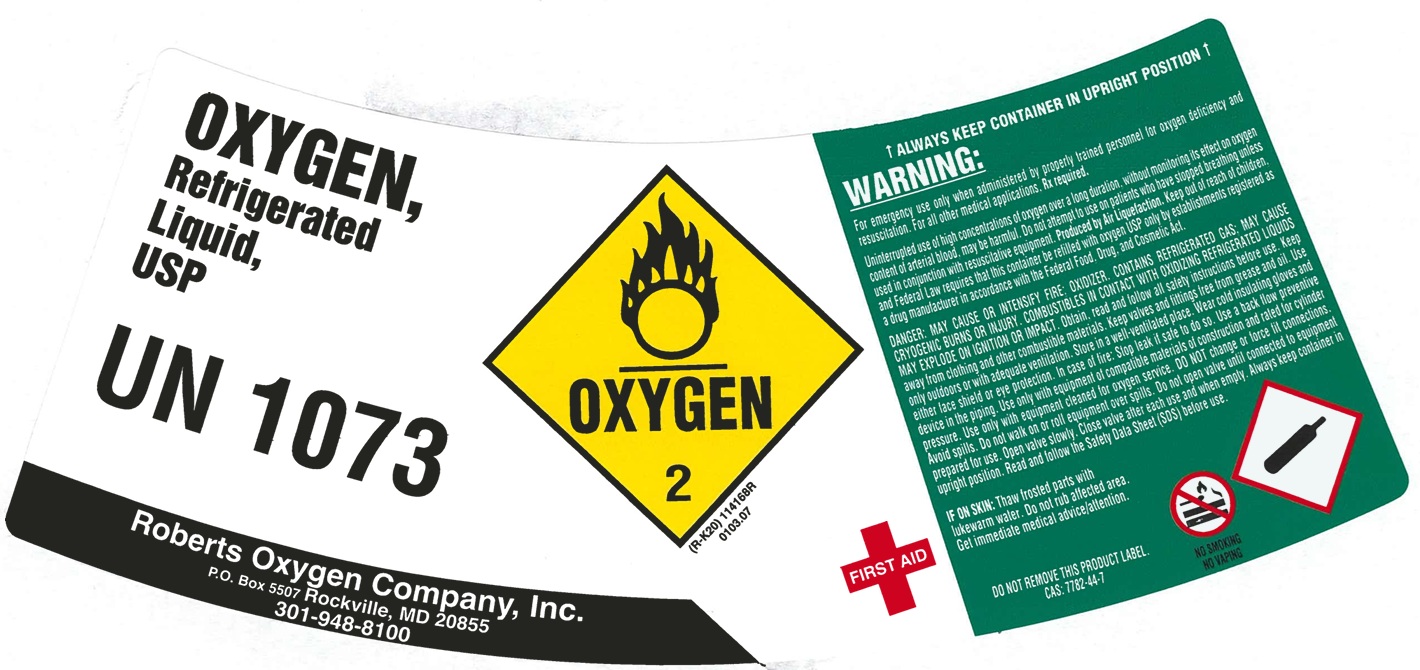 DRUG LABEL: Oxygen
NDC: 46123-002 | Form: GAS
Manufacturer: Roberts Oxygen Company, Inc.
Category: prescription | Type: HUMAN PRESCRIPTION DRUG LABEL
Date: 20251117

ACTIVE INGREDIENTS: OXYGEN 990 mL/1 L

Oxygen, Liquid USP-002

PACKAGE LABEL

OXYGEN, Refrigerated Liquid, USP

UN 1073

Roberts Oxygen Company, Inc.

PO Box 5507 Rockville, MD 20855

301-948-8100

ALWAYS KEEP CONTAINER IN UPRIGHT POSITION

WARNING: For emergency use only when administered by properly trained personnel for oxygen deficiency and resuscitation. For all other medical applications, Rx required.

Uninterrupted use of high concentrations of oxygen over a long duration, without monitoring its effect on oxygen content of arterial blood, may be harmful. Do not attempt to use on patients who have stopped breathing unless used in conjunction with resuscitative equipment. Produced by Air Liquefaction. Keep out of reach of children, and Federal Law requires that this container be refilled with oxygen USP only by establishments registered as a drug manufacturer in accordance with the Federal Food, Drug, and Cosmetic Act.

DANGER: MAY CAUSE OR INTENSIFY FIRE; OXIDIZER. CONTAINS REFRIGERATED GAS; MAY CAUSE CRYOGENIC BURNS OR INJURY. COMBUSTIBLES IN CONTACT WITH OXIDIZING REFRIGERATED LIQUIDS MAY EXPLODE ON IGINITION OR IMPACT. Obtain, read and follow all safety instructions before use. Keep away from clothing and other combustible materials. Keep valves and fittings free from grease and oil. Use only outdoors or with adequate ventilation. Store in a well-ventilated place. Wear cold insulating gloves and either face shield or eye protection. In case of fire: Stop leak if safe to do so. Use a back flow preventive device in the piping. Use only with equipment of compatible materials of construction and rated for cylinder pressure. Use only with equipment cleaned for oxygen service. DO NOT change or force fit connections. Avoid spills. Do not walk on or roll equipment over spills. Do not open valve until connected to equipment prepared for use. Open valve slowly. Close valve after each use and when empty. Always keep container in upright position. Read and follow the Safety Data Sheet (SDS) before use.

FIRST AID: IF ON SKIN: Thaw frosted parts with lukewarm water. Do not rub affected area. Get immediate medical advice/attention.

DO NOT REMOVE THIS PRODUCT LABEL.

CAS: 7782-44-7

NO SMOKING

NO VAPING